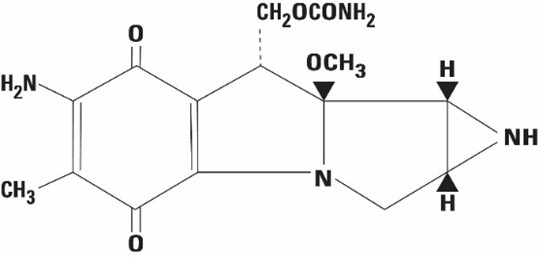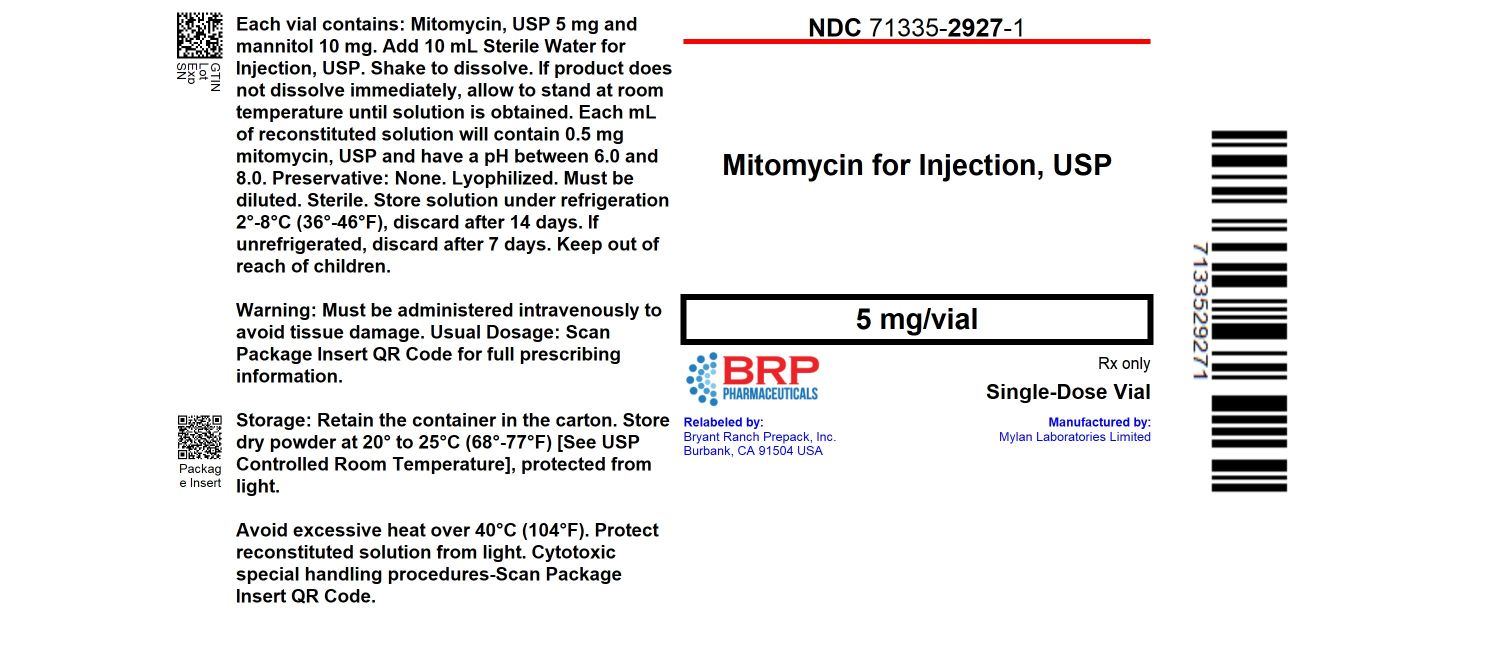 DRUG LABEL: Mitomycin
NDC: 71335-2927 | Form: INJECTION, POWDER, LYOPHILIZED, FOR SOLUTION
Manufacturer: Bryant Ranch Prepack
Category: prescription | Type: HUMAN PRESCRIPTION DRUG LABEL
Date: 20251111

ACTIVE INGREDIENTS: MITOMYCIN 5 mg/10 mL
INACTIVE INGREDIENTS: MANNITOL

MITOMYCIN FOR INJECTION USP, 5 mg/vial
NOVAPLUS®

Rx only

WARNING

Mitomycin should be administered under the supervision of a qualified physician experienced in the use of cancer chemotherapeutic agents. Appropriate management of therapy and complications is possible only when adequate diagnostic and treatment facilities are readily available.

Bone marrow suppression, notably thrombocytopenia and leukopenia, which may contribute to overwhelming infections in an already compromised patient, is the most common and severe of the toxic effects of mitomycin (see WARNINGS and ADVERSE REACTIONS sections).

Hemolytic Uremic Syndrome (HUS) a serious complication of chemotherapy, consisting primarily of microangiopathic hemolytic anemia, thrombocytopenia, and irreversible renal failure has been reported in patients receiving systemic mitomycin. The syndrome may occur at any time during systemic therapy with mitomycin as a single agent or in combination with other cytotoxic drugs, however, most cases occur at doses ≥60 mg of mitomycin. Blood product transfusion may exacerbate the symptoms associated with this syndrome.

The incidence of the syndrome has not been defined.

DESCRIPTION

Mitomycin, USP (also known as Mitomycin and/or Mitomycin-C) is an antibiotic isolated from the broth of Streptomyces caespitosus which has been shown to have antitumor activity. The compound is heat stable, has a high melting point, and is freely soluble in organic solvents.

Mitomycin for Injection, USP is a sterile dry mixture of mitomycin, USP and mannitol, which when reconstituted with Sterile Water for Injection provides a solution for intravenous administration. Each vial contains either mitomycin, USP 5 mg and mannitol 10 mg, or mitomycin, USP 20 mg and mannitol 40 mg, or mitomycin, USP 40 mg and mannitol 80 mg. Each mL of reconstituted solution will contain 0.5 mg mitomycin, USP and have a pH between 6.0 and 8.0.

Mitomycin, USP is a blue-violet crystalline powder with the molecular formula of C15H18N4O5, and a molecular weight of 334.33. Its chemical name is 7-amino-9α-methoxymitosane and it has the following structural formula;

CLINICAL PHARMACOLOGY

Mitomycin selectively inhibits the synthesis of deoxyribonucleic acid (DNA). The guanine and cytosine content correlates with the degree of mitomycin-induced cross-linking. At high concentrations of the drug, cellular RNA and protein synthesis are also suppressed.

In humans, mitomycin is rapidly cleared from the serum after intravenous administration. Time required to reduce the serum concentration by 50% after a 30 mg bolus injection is 17 minutes. After injection of 30 mg, 20 mg, or 10 mg Intravenous., the maximal serum concentrations were 2.4 mcg/mL, 1.7 mcg/mL, and 0.52 mcg/mL, respectively. Clearance is effected primarily by metabolism in the liver, but metabolism occurs in other tissues as well. The rate of clearance is inversely proportional to the maximal serum concentration because, it is thought, of saturation of the degradative pathways.

Approximately 10% of a dose of mitomycin is excreted unchanged in the urine. Since metabolic pathways are saturated at relatively low doses, the percent of a dose excreted in urine increases with increasing dose.

In children, excretion of intravenously administered mitomycin is similar.

Animal Toxicology

Mitomycin has been found to be carcinogenic in rats and mice. At doses approximating the recommended clinical dose in man, it produces a greater than 100 percent increase in tumor incidence in male Sprague-Dawley rats, and a greater than 50 percent increase in tumor incidence in female Swiss mice.

INDICATIONS AND USAGE

Mitomycin for Injection, USP is not recommended as single-agent, primary therapy. It has been shown to be useful in the therapy of disseminated adenocarcinoma of the stomach or pancreas in proven combinations with other approved chemotherapeutic agents and as palliative treatment when other modalities have failed. Mitomycin is not recommended to replace appropriate surgery and/or radiotherapy.

CONTRAINDICATIONS

Mitomycin is contraindicated in patients who have demonstrated a hypersensitive or idiosyncratic reaction to it in the past.

Mitomycin is contraindicated in patients with thrombocytopenia, coagulation disorder, or an increase in bleeding tendency due to other causes.

WARNINGS

Patients being treated with mitomycin must be observed carefully and frequently during and after therapy.

The use of mitomycin results in a high incidence of bone marrow suppression, particularly thrombocytopenia and leukopenia. Therefore, the following studies should be obtained repeatedly during therapy and for at least eight weeks following therapy: platelet count, white blood cell count, differential, and hemoglobin. The occurrence of a platelet count below 100,000/mm^3 or a WBC below 4,000/mm^3 or a progressive decline in either is an indication to withhold further therapy until blood counts have recovered above these levels.

Patients should be advised of the potential toxicity of this drug, particularly bone marrow suppression.

Deaths have been reported due to septicemia as a result of leukopenia due to the drug.

Patients receiving mitomycin should be observed for evidence of renal toxicity. Mitomycin should not be given to patients with a serum creatinine greater than 1.7 mg percent.

Usage in Pregnancy

Safe use of mitomycin in pregnant women has not been established. Teratological changes have been noted in animal studies. The effect of mitomycin on fertility is unknown.

PRECAUTIONS

Acute shortness of breath and severe bronchospasm have been reported following the administration of vinca alkaloids in patients who had previously or simultaneously received mitomycin. The onset of this acute respiratory distress occurred within minutes to hours after the vinca alkaloid injection. The total number of doses for each drug has varied considerably. Bronchodilators, steroids and/or oxygen have produced symptomatic relief.

A few cases of adult respiratory distress syndrome have been reported in patients receiving mitomycin in combination with other chemotherapy and maintained at FlO2 concentrations greater than 50% perioperatively. Therefore, caution should be exercised using only enough oxygen to provide adequate arterial saturation since oxygen itself is toxic to the lungs. Careful attention should be paid to fluid balance and overhydration should be avoided.

Bladder fibrosis/contraction has been reported with intravesical administration (not an approved route of administration), which in rare cases has required cystectomy.

Nursing Mothers

It is not known if mitomycin is excreted in human milk. Because many drugs are excreted in human milk and because of the potential for serious adverse reactions in nursing infants from mitomycin, it is recommended that nursing be discontinued when receiving mitomycin therapy.

Pediatric Use

Safety and effectiveness in pediatric patients have not been established.

Geriatric Use

Insufficient data from clinical studies of mitomycin are available for patients 65 years of age and older to determine whether they respond differently than younger patients. Postmarketing surveillance suggests that elderly patients may be more susceptible than younger patients to injection site reactions (see ADVERSE REACTIONS: Integument and Mucous Membrane Toxicity) and hypersensitivity reactions. In general, caution should be exercised when prescribing to elderly patients, reflecting the greater frequency of decreased hepatic, renal, or cardiac function, and of concomitant disease or other drug therapy.

ADVERSE REACTIONS

Bone Marrow Toxicity

This was the most common and most serious toxicity, occurring in 605 of 937 patients (64.4%). Thrombocytopenia and/or leukopenia may occur anytime within 8 weeks after onset of therapy with an average time of 4 weeks. Recovery after cessation of therapy was within 10 weeks. About 25% of the leukopenic or thrombocytopenic episodes did not recover. Mitomycin produces cumulative myelosuppression.

Integument and Mucous Membrane Toxicity

This has occurred in approximately 4% of patients treated with mitomycin. Cellulitis at the injection site has been reported and is occasionally severe. Stomatitis and alopecia also occur frequently. Rashes are rarely reported. The most important dermatological problem with this drug, however, is the necrosis and consequent sloughing of tissue which results if the drug is extravasated during injection. Extravasation may occur with or without an accompanying stinging or burning sensation and even if there is adequate blood return when the injection needle is aspirated. There have been reports of delayed erythema and/or ulceration occurring either at or distant from the injection site, weeks to months after mitomycin, even when no obvious evidence of extravasation was observed during administration. Skin grafting has been required in some of the cases. Elderly patients may be more susceptible than younger patients to injection site reactions (see PRECAUTIONS: Geriatric Use).

Renal Toxicity

2% of 1,281 patients demonstrated a statistically significant rise in creatinine. There appeared to be no correlation between total dose administered or duration of therapy and the degree of renal impairment.

Pulmonary Toxicity

This has occurred infrequently but can be severe and may be life-threatening. Dyspnea with a nonproductive cough and radiographic evidence of pulmonary infiltrates may be indicative of mitomycin-induced pulmonary toxicity. If other etiologies are eliminated, mitomycin therapy should be discontinued. Steroids have been employed as treatment of this toxicity, but the therapeutic value has not been determined. A few cases of adult respiratory distress syndrome have been reported in patients receiving mitomycin in combination with other chemotherapy and maintained at FlO2 concentrations greater than 50% perioperatively.

Hemolytic Uremic Syndrome (HUS)

This serious complication of chemotherapy, consisting primarily of microangiopathic hemolytic anemia (hematocrit ≤25%), thrombocytopenia (≤100,000/mm^3), and irreversible renal failure (serum creatinine ≥1.6 mg/dL) has been reported in patients receiving systemic mitomycin. Microangiopathic hemolysis with fragmented red blood cells on peripheral blood smears has occurred in 98% of patients with the syndrome. Other less frequent complications of the syndrome may include pulmonary edema (65%), neurologic abnormalities (16%), and hypertension. Exacerbation of the symptoms associated with HUS has been reported in some patients receiving blood product transfusions. A high mortality rate (52%) has been associated with this syndrome.

The syndrome may occur at any time during systemic therapy with mitomycin as a single agent or in combination with other cytotoxic drugs. Less frequently, HUS has also been reported in patients receiving combinations of cytotoxic drugs not including mitomycin. Of 83 patients studied, 72 developed the syndrome at total doses exceeding 60 mg of mitomycin. Consequently, patients receiving ≥60 mg of mitomycin should be monitored closely for unexplained anemia with fragmented cells on peripheral blood smear, thrombocytopenia, and decreased renal function.

The incidence of the syndrome has not been defined.

Therapy for the syndrome is investigational.

Cardiac Toxicity

Congestive heart failure, often treated effectively with diuretics and cardiac glycosides, has rarely been reported. Almost all patients who experienced this side effect had received prior doxorubicin therapy.

Acute Side Effects Due to Mitomycin were fever, anorexia, nausea, and vomiting. They occurred in about 14% of 1,281 patients.

Other

Headache, blurring of vision, confusion, drowsiness, syncope, fatigue, edema, thrombophlebitis, hematemesis, diarrhea, and pain. These did not appear to be dose related and were not unequivocally drug related. They may have been due to the primary or metastatic disease processes. Malaise and asthenia have been reported as part of postmarketing surveillance. Bladder fibrosis/contraction has been reported with intravesical administration (see PRECAUTIONS).

To report SUSPECTED ADVERSE REACTIONS, contact RK Pharma Inc. at 1-844-757-4276 (1-844-4-RKPHARM). or FDA at 1-800-FDA-1088 or www.fda.gov/medwatch.

DOSAGE AND ADMINISTRATION

Parenteral drug products should be inspected visually for particulate matter and discoloration prior to administration whenever solution and container permit.

Mitomycin should be given intravenously only, using care to avoid extravasation of the compound. If extravasation occurs, cellulitis, ulceration, and slough may result.

Each vial contains mitomycin, USP 5 mg and mannitol 10 mg. To administer, add Sterile Water for Injection, 10 mL. Shake to dissolve. If product does not dissolve immediately, allow to stand at room temperature until solution is obtained.

After full hematological recovery (see guide to dosage adjustment) from any previous chemotherapy, the following dosage schedule may be used at 6 to 8 week intervals:

20 mg/m^2 intravenously as a single dose via a functioning intravenous catheter.

Because of cumulative myelosuppression, patients should be fully reevaluated after each course of mitomycin, and the dose reduced if the patient has experienced any toxicities. Doses greater than 20 mg/m^2 have not been shown to be more effective, and are more toxic than lower doses.

The following schedule is suggested as a guide to dosage adjustment:

Nadir After Prior Dose
Leukocytes/mm ^3 | Platelets/mm ^3 | Percentage of Prior Dose To Be Given
>4000 | >100,000 | 100%
3000-3999 | 75,000-99,999 | 100%
2000-2999 | 25,000-74,999 | 70%
<2000 | <25,000 | 50%

No repeat dosage should be given until leukocyte count has returned to 4000/mm ^3 and a platelet count to 100,000/mm ^3.

When mitomycin is used in combination with other myelosuppressive agents, the doses should be adjusted accordingly. If the disease continues to progress after two courses of mitomycin, the drug should be stopped since chances of response are minimal.

STABILITY

1. Unreconstituted mitomycin stored at room temperature is stable for the lot life indicated on the package. Avoid excessive heat (over 40°C, 104°F).
2. Reconstituted with Sterile Water for Injection to a concentration of 0.5 mg per mL, mitomycin is stable for 14 days refrigerated or 7 days at room temperature.
3. Diluted in various intravenous fluids at room temperature, to a concentration of 20 to 40 micrograms per mL:
  Intravenous Fluid | Stability
  0.9% Sodium Chloride Injection | 12 hours
  Sodium Lactate Injection | 24 hours
4. The combination of mitomycin (5 mg to 15 mg) and heparin (1,000 units to 10,000 units) in 30 mL of 0.9% Sodium Chloride Injection is stable for 48 hours at room temperature.

Procedures for proper handling and disposal of anticancer drugs should be considered. Several guidelines on this subject have been published.^1-8 There is no general agreement that all of the procedures recommended in the guidelines are necessary or appropriate.

HOW SUPPLIED

Mitomycin for injection, USP

NDC: 71335-2927-1: 5 mg; individually-boxed amber vial

Storage: Store dry powder at 20° to 25°C (68° to 77°F) [See USP Controlled Room Temperature.], protected from light. Avoid excessive heat, over 40°C (104°F). Protect reconstituted solution from light. Store solution under refrigeration 2° to 8°C (36° to 46°F), discard after 14 days. If unrefrigerated, discard after 7 days.

Repackaged/Relabeled by:
Bryant Ranch Prepack, Inc.
Burbank, CA 91504

References

1. ONS Clinical Practice Committee. Cancer Chemotherapy Guidelines and Recommendations for Practice Pittsburgh, PA: Oncology Nursing Society; 1999:32-41.
2. Recommendations for the safe handling of parenteral antineoplastic drugs. Washington, DC: Division of Safety, National Institutes of Health; 1983. US Dept of Health and Human Services, Public Health Service publication NIH 83-2621.
3. AMA Council on Scientific Affairs. Guidelines for handling parenteral antineoplastics. JAMA. 1985;253:1590-1591.
4. National Study Commission on Cytotoxic Exposure. – Recommendations for handling cytotoxic agents. 1987. Available from Louis P. Jeffrey, Chairman, National Study Commission on Cytotoxic Exposure. Massachusetts College of Pharmacy and Allied Health Sciences, 179 Longwood Avenue, Boston, MA 02115.
5. Clinical Oncological Society of Australia. Guidelines and recommendations for safe handling of antineoplastic agents. Med J Australia. 1983;1:426-428.
6. Jones RB, Frank R, Mass T. Safe handling of chemotherapeutic agents: a report from the Mount Sinai Medical Center. CA-A Cancer J for Clin. 1983;33:258-263.
7. American Society of Hospital Pharmacists. ASHP technical assistance bulletin on handling cytotoxic and hazardous drugs. Am J Hosp Pharm. 1990;47:1033-1049.
8. Controlling Occupational Exposure to Hazardous Drugs. (OSHA Work-Practice Guidelines.). Am J Health SystPharm. 1996;53:1669-1685.

DECEMBER 2021
PI-152-00-NP

Distributed by

Archis Pharma LLC
Piscataway, NJ 08854

NOVAPLUS is a registered trademarks of of Vizient, Inc.

1033045

PACKAGE LABEL

Mitomycin 5 mg/vial Injection #10 mL